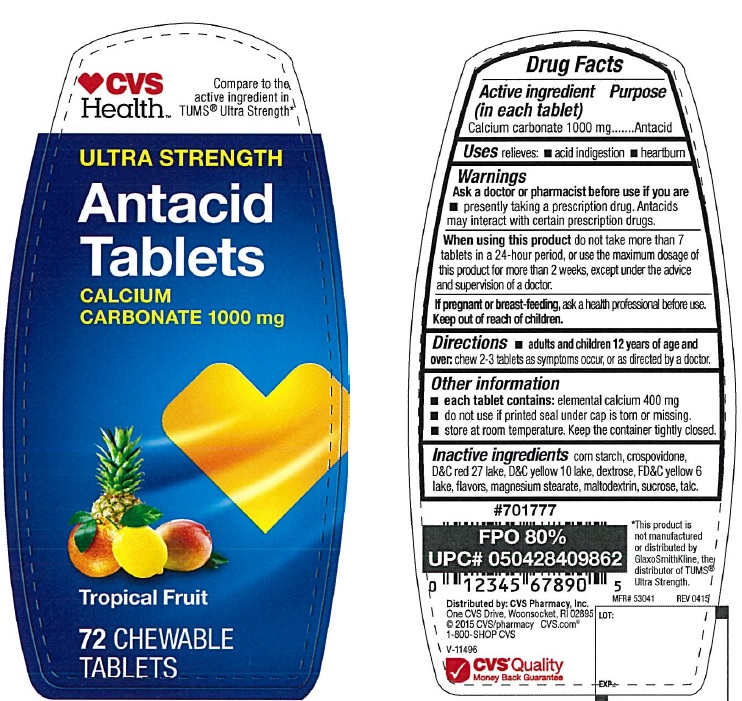 DRUG LABEL: Ultra Strength Antacid Tropical fruit
NDC: 69842-371 | Form: TABLET, CHEWABLE
Manufacturer: CVS
Category: otc | Type: HUMAN OTC DRUG LABEL
Date: 20171003

ACTIVE INGREDIENTS: CALCIUM CARBONATE 1000 mg/1 1
INACTIVE INGREDIENTS: STARCH, CORN; CROSPOVIDONE; D&C RED NO. 27; D&C YELLOW NO. 10; DEXTROSE; FD&C YELLOW NO. 6; MAGNESIUM STEARATE; MALTODEXTRIN; SUCROSE; TALC

CVS Ultra Strength Antacid Tablets Tropical Fruit

Active ingredient (in each tablet)

Calcium carbonate 1000 mg

Purpose

Antacid

Uses

relieves

- acid indigestion
- heartburn

Warnings

Ask a doctor or pharmacist before use if you are

presently taking a prescription drug. Antacids may interact with certain prescription drugs.

When using this product

do not take more than 7 tablets in a 24 hour period, or use the maximum dosage of this product for more than 2 weeks, except under the advice and supervision of a doctor.

If pregnant or breast feeding, ask a health professional before use.

Keep out of reach of children.

Directions

- adults and children 12 years of age and over: chew 2-3 tablets as symptoms occur, or as directed by a doctor.

Other information

- each tablet contains: elemental calcium 400 mg
- do not use if printed seal under cap is torn or missing.
- store at room temperature.

Inactive ingredients

corn starch, crospovidone, D&C red 27 lake, D&C yellow 10 lake, dextrose, FD&C yellow 6 lake, flavors, magnesium stearate, maltodextrin, sucrose, talc

PDP

Ultra strength Antacid Tablets

Calcium carbonate 1000 mg

Tropical Fruit

72 Chewable Tablets